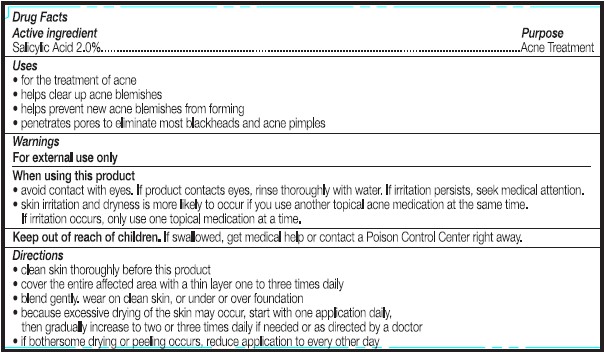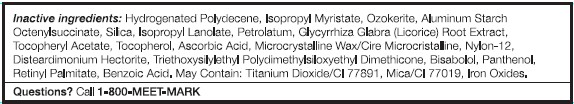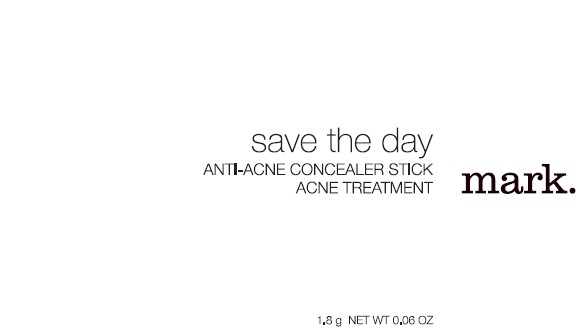 DRUG LABEL: mark. save the day
NDC: 10096-0203 | Form: STICK
Manufacturer: Avon Products, Inc.
Category: otc | Type: HUMAN OTC DRUG LABEL
Date: 20120522

ACTIVE INGREDIENTS: Salicylic Acid 36 mg/1.8 g

Drug Facts

Active ingredient Purpose
Salicylic Acid 2.0%....................Acne Treatment

Purpose
........Acne Treatment

Uses
• for the treatment of acne
• helps clear up acne blemishes
• helps prevent new acne blemishes from forming
• penetrates pores to eliminate most blackheads and acne pimples

Warnings
For external use only

When using this product
• avoid contact with eyes. If product contacts eyes, rinse thoroughly with water. If irritation persists, seek medical attention.
• skin irritation and dryness is more likely to occur if you use another topical acne medication at the same time. If irritation occurs, only use one topical medication at a time.

Keep out of reach of children. If swallowed, get medical help or contact a Poison Control Center right away.

Directions
• cleanse skin thoroughly before this product
• cover the entire affected area with a thin layer one to three times daily
• blend gently. Wear on clean skin, or under or over foundation

• because excessive drying of the skin may occur, start with one application daily, then gradually increase to two or three times daily if needed or as directed by a doctor

• if bothersome dryness or peeling occurs, reduce application to every other day

Inactive Ingredients:

HYDROGENATED POLYDECENE
ISOPROPYL MYRISTATE
OZOKERITE
ALUMINUM STARCH OCTENYLSUCCINATE
SILICA
ISOPROPYL LANOLATE
PETROLATUM
GLYCYRRHIZA GLABRA (LICORICE) ROOT EXTRACT
TOCOPHERYL ACETATE
TOCOPHEROL
ASCORBIC ACID
MICROCRYSTALLINE WAX/CIRE MICROCRISTALLINE
NYLON-12
DISTEARDIMONIUM HECTORITE
TRIETHOXYSILYLETHYL POLYDIMETHYLSILOXYETHYL DIMETHICONE
BISABOLOL
PANTHENOL
RETINYL PALMITATE
BENZOIC ACID

MAY CONTAIN:
TITANIUM DIOXIDE/CI 77891
MICA/CI 77019
IRON OXIDES

Questions? Call 1-800-MEET-MARK